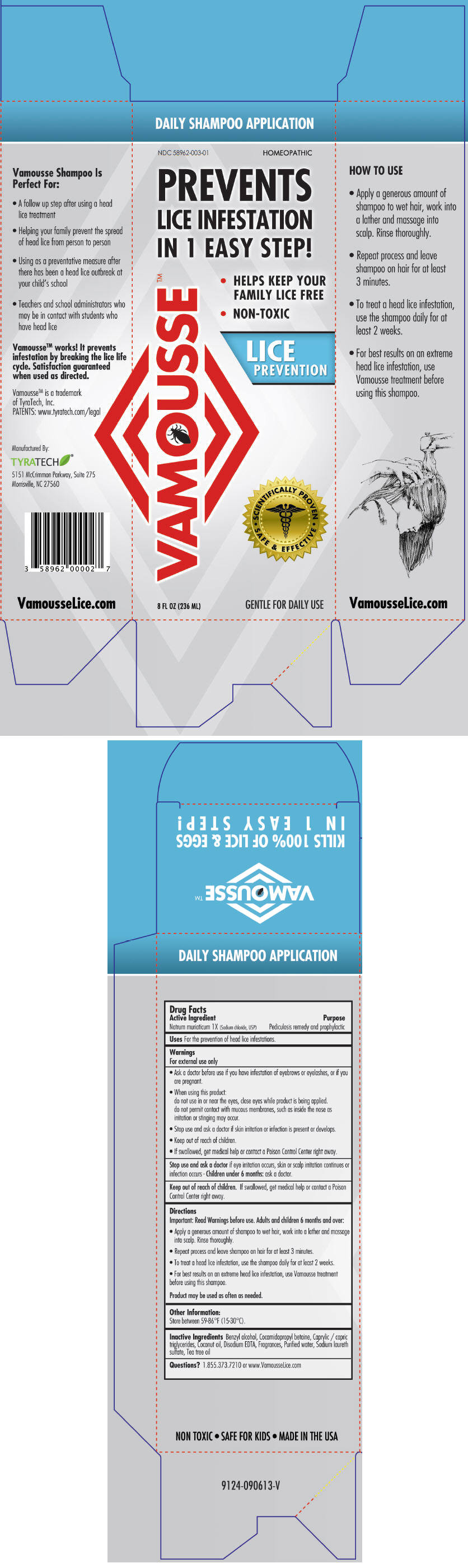 DRUG LABEL: Vamousse Lice Prevention
NDC: 58962-003 | Form: SHAMPOO
Manufacturer: TyraTech, Inc.
Category: homeopathic | Type: HUMAN OTC DRUG LABEL
Date: 20140117

ACTIVE INGREDIENTS: SODIUM CHLORIDE 1 [hp_X]/1 mL
INACTIVE INGREDIENTS: BENZYL ALCOHOL; COCAMIDOPROPYL BETAINE; MEDIUM-CHAIN TRIGLYCERIDES; COCONUT OIL; EDETATE DISODIUM; GERANIOL; WATER; SODIUM LAURETH-3 SULFATE; TEA TREE OIL

Vamousse™ Lice Prevention Shampoo

Active Ingredient

Natrum muriaticum 1X (Sodium chloride, USP)

Purpose

Pediculosis remedy and prophylactic

Uses

For the prevention of head lice infestations

Warnings

For external use only

- Ask a doctor before use if you have infestation of eyebrows or eyelashes, or if you are pregnant.

- When using this product:
  do not use in or near the eyes, close eyes while product is being applied.
  do not permit contact with mucous membranes, such as inside the nose as irritation or stinging may occur.

- Stop use and ask a doctor if skin irritation or infection is present or develops.

- Keep out of reach of children.
- If swallowed, get medical help or contact a Poison Control Center right away.

Stop use and ask a doctor if eye irritation occurs, skin or scalp irritation continues or infection occurs – Children under 6 months: ask a doctor.

Keep out of reach of children. If swallowed, get medical help or contact a Poison Control Center right away.

Directions

Important: Read Warnings before use. Adults and children 6 months and over:

- Apply a generous amount of shampoo to wet hair, work into a lather and massage into scalp. Rinse thoroughly.
- Repeat process and leave shampoo on hair for at least 3 minutes.
- To treat head lice infestation, use the shampoo daily for at least 2 weeks.
- For best results on an extreme head lice infestation, use Vamousse treatment before using shampoo.

Product may be used as often as needed.

Other Information

Store between 59-86°F (15-30°C)

Inactive Ingredients

Benzyl alcohol, Cocomidopropyl betaine, Caprylic / capric triglycerides, Coconut oil, Disodium EDTA, Fragrances, Purified Water, Sodium laureth sulfate, Tea tree oil.

Questions?

1.855.373.7210 or www.VamousseLice.com

Manufactured By:
TYRATECH
5151 McCrimmon Parkway, Suite 275
Morrisville, NC 27560

PRINCIPAL DISPLAY PANEL - 236 ML Bottle Carton

DAILY SHAMPOO APPLICATION

NDC 58962-003-01
HOMEOPATHIC

PREVENTS
LICE INFESTATION
IN 1 EASY STEP!

- HELPS KEEP YOUR FAMILY LICE FREE
- NON-TOXIC

VAMOUSSE™

LICE PREVENTION
SCIENTIFICALLY PROVEN SAFE & EFFECTIVE

8 FL OZ (236 ML)
GENTLE FOR DAILY USE